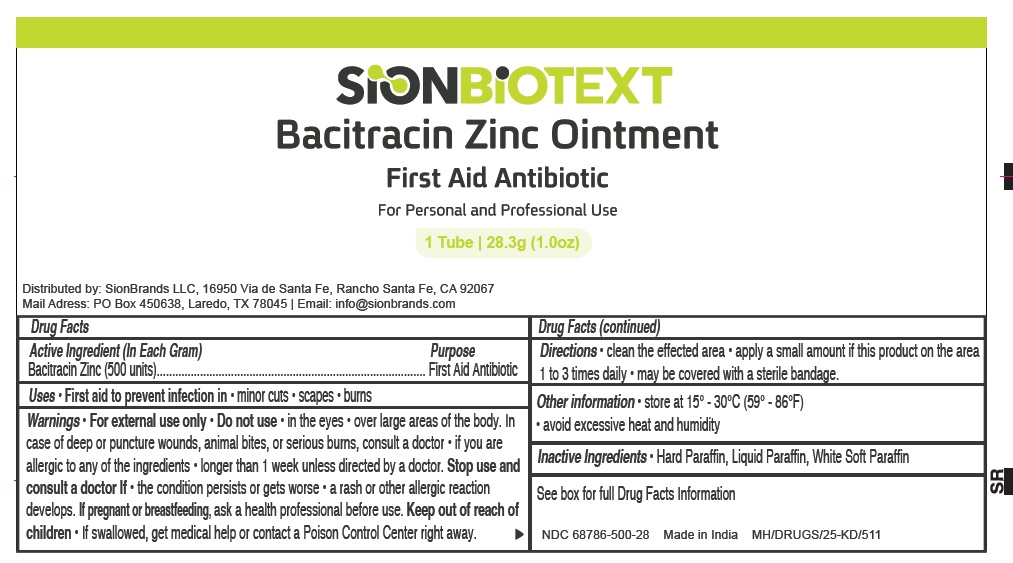 DRUG LABEL: Sion Biotext Bacitracin Zinc
NDC: 68786-500 | Form: OINTMENT
Manufacturer: Sion Biotext Medical Ltd
Category: otc | Type: HUMAN OTC DRUG LABEL
Date: 20250612

ACTIVE INGREDIENTS: BACITRACIN ZINC 500 [iU]/1 g
INACTIVE INGREDIENTS: PARAFFIN; WHITE PETROLATUM; MINERAL OIL

Bacitracin Zinc Ointment

Active Ingredient (In Each Gram)

Bacitracin Zinc (500 units)

Purpose

First Aid Antibiotic

Uses

First aid to prevent infection in

- minor cuts
- scrapes
- burns

Warnings section

For external use only

Do not use

- in the eyes
- over large areas of the body. In case of deep or puncture wounds, animal bites or serious burns, consult a doctor
- if you are allergic to any ingredient
- longer than 1 week unless directed by a doctor
- If seal is torn or if the tube is damaged

Stop use and ask a doctor if

- the condition persists or gets worse
- a rash or other allergic reaction develops

keep out of reach of children

If swallowed, get medical help or contact a posion control center right away.

if pregnant or breast feeding

ask a health professional before use

Directions

- Clean the affected area
  - apply a small amount of this product (an amount equal to the surface area of the tip of a finger) an the area 1 to 3 times a day
  - may be covered with a sterile bandage

Other Information

- store at 15°-30°C (59°-86°F)
- avoid excessive heat and humidity

Inactive Ingredients

Hard Paraffin, Liquid Paraffin, White Soft Paraffin

Questions

info@sionbrands.com

Distributed by

SionBrands LLC

16950 Bia de Santa Fe, Rancho Fe, CA, 92067

Mail Address: PO Box 450638,Laredo, TX, 78045

Email: info@sionbrands.com

PACKAGE LABEL

NDC 68786-500-01

SION BIOTEXT

Bacitracin Zinc Ointment

First aid to prevent infection in Minor cuts | Scrapes | Burns

For Personal and Professional Use

Made in India

Net Wt: 1.0 oz (28.3g)